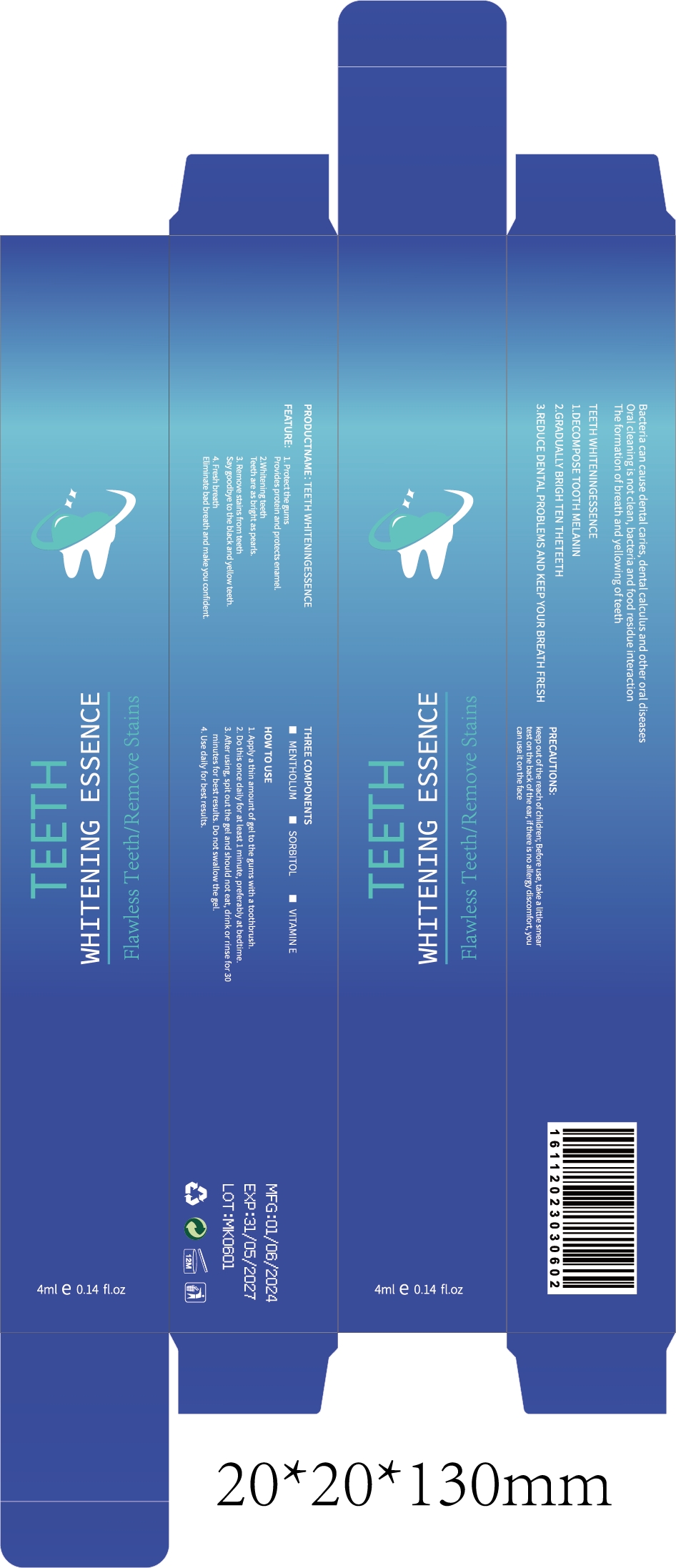 DRUG LABEL: TEETH WHITENINGESSENCE
NDC: 84732-023 | Form: LIQUID
Manufacturer: Dongguan Haiyi Technology Co.,Ltd.
Category: otc | Type: HUMAN OTC DRUG LABEL
Date: 20240928

ACTIVE INGREDIENTS: .ALPHA.-TOCOPHEROL 1 mg/4 mL; MENTHOL 1 mg/4 mL
INACTIVE INGREDIENTS: SORBITOL

Active ingredient

Mentholum

Vitamin E

Inactive ingredient

Sorbitol

Purpose section

1. Protect the gumsProvides protein and protects enamel.
2.Whitening teethTeeth are as bright as pearls.
3. Remove stains from teethSay goodbye to the black and yellow teeth.
4. Fresh breathEliminate bad breath and make you confident

waring

keep out of the reach of children; Before use, take a little smeartest on the back of the ear, if there is no allergy discomfort, youcan use it on the face

stop use

This product may cause allergic reactions in asmall number of people.
lf youexperience any discomfort,please stop using it immediately.

not use

Not suitable for use by children, pregnantor breastfeeding people.

OUT OF CHILDREN

KEEP THE PRODUCT OUT OF REACH OF CHILDREN to

HOW TO USE

1. Apply a thin amount of gel to the gums with a toothbrush.

2. Do this once daily for at least 1 minute, preferably at bedtime.

3. After using, spit out the gel and should not eat, drink or rinse for 30minutes for best results. Do not swallow the gel.

4. Use daily for best results.

Dosage

Once a day in the morning and evening